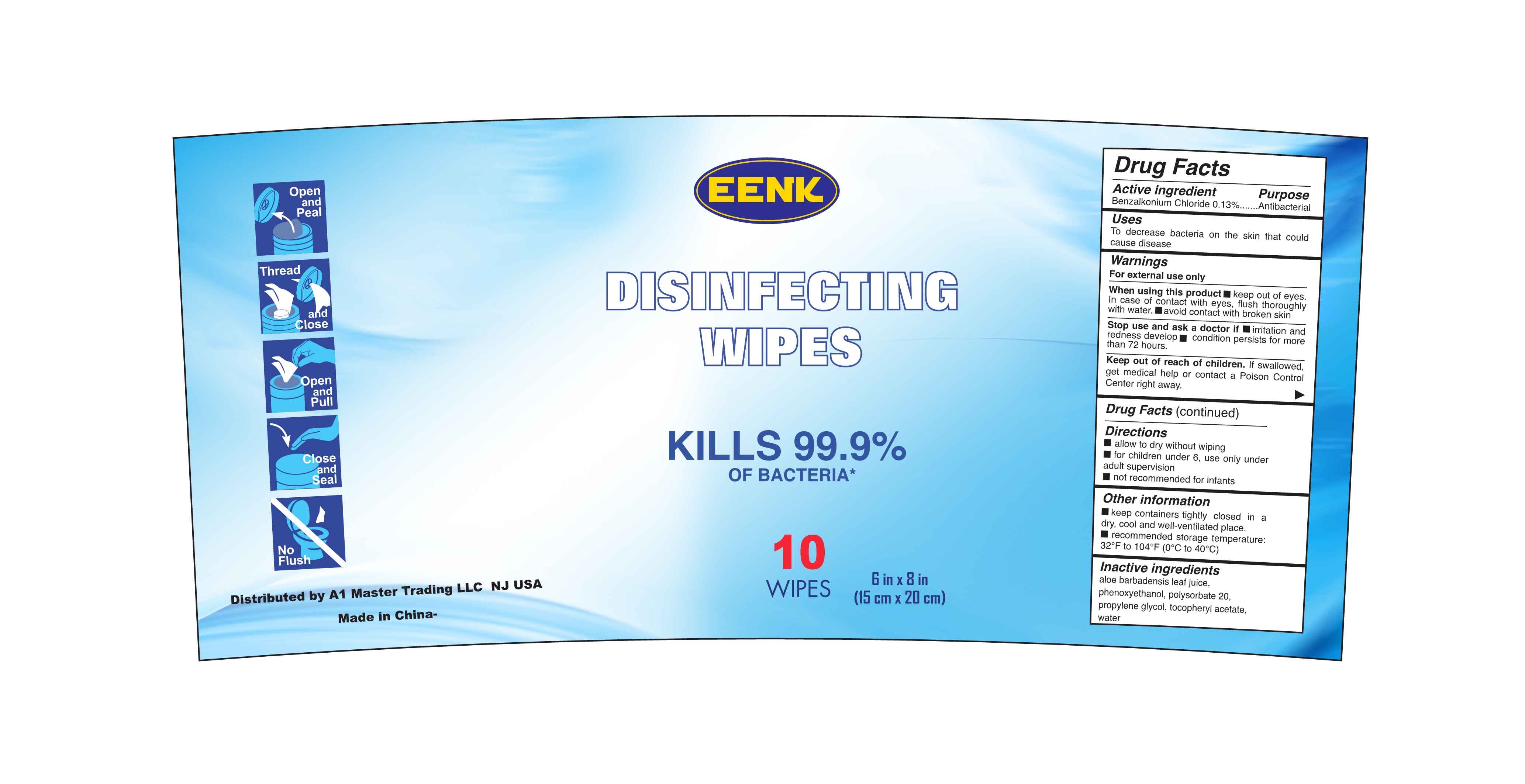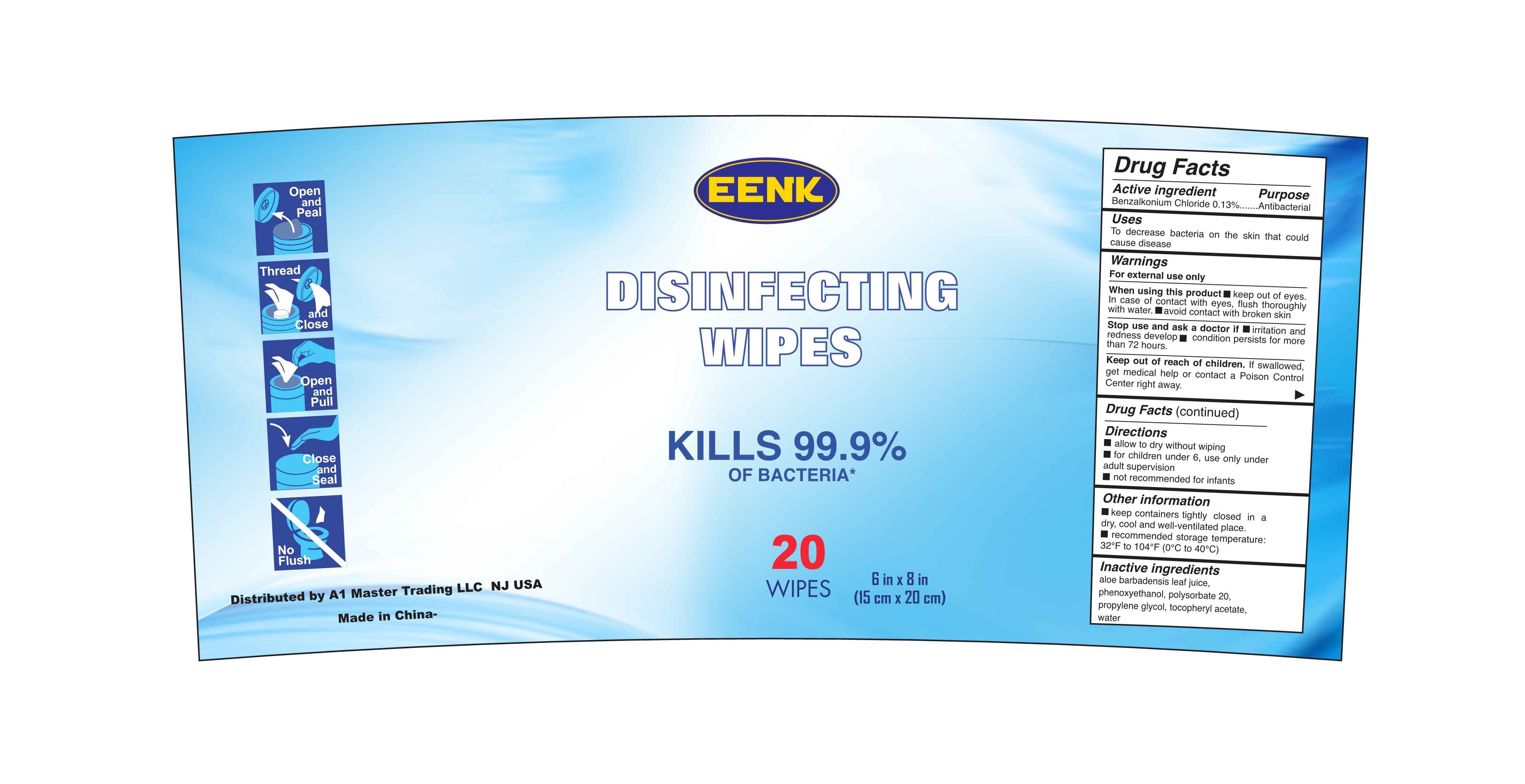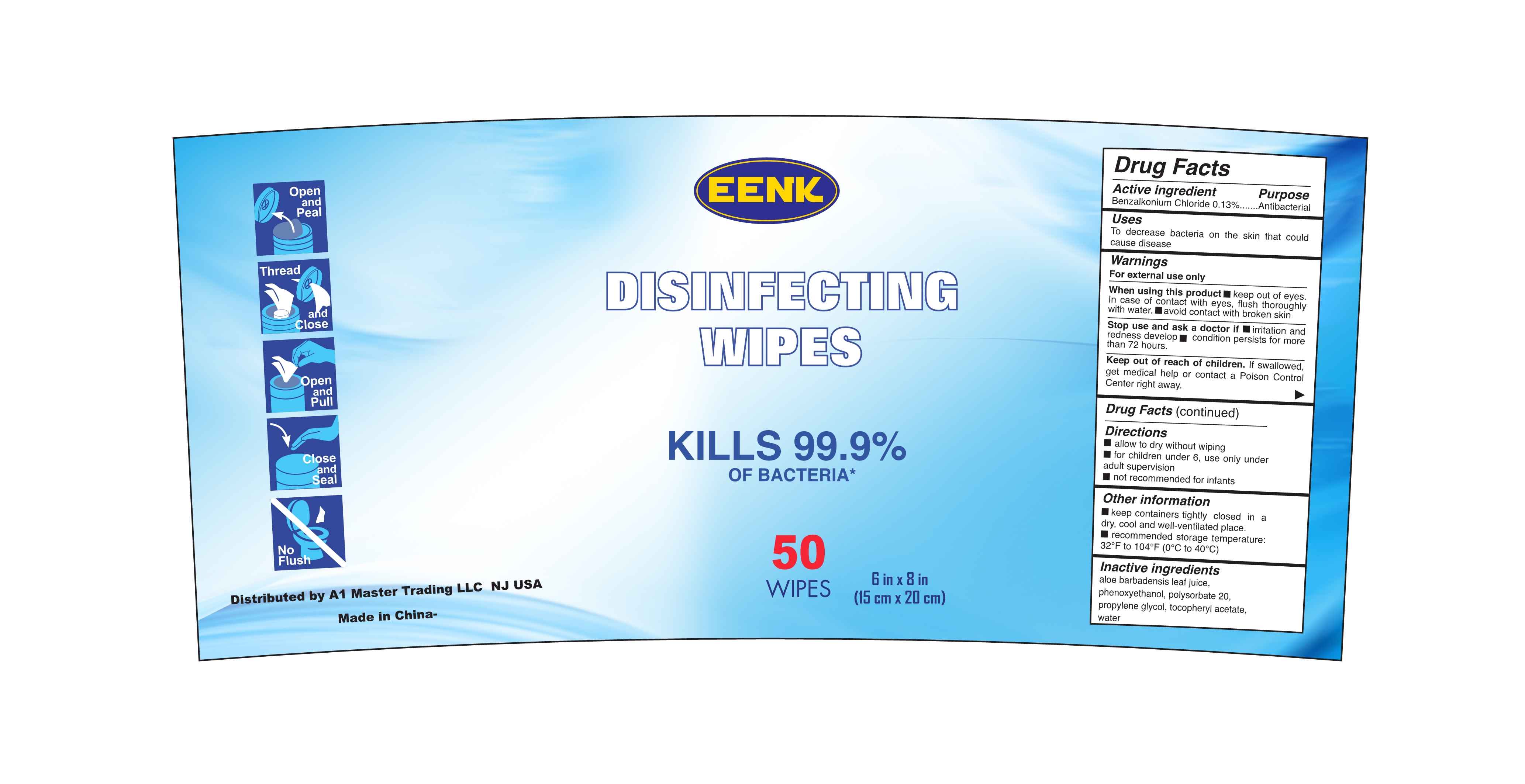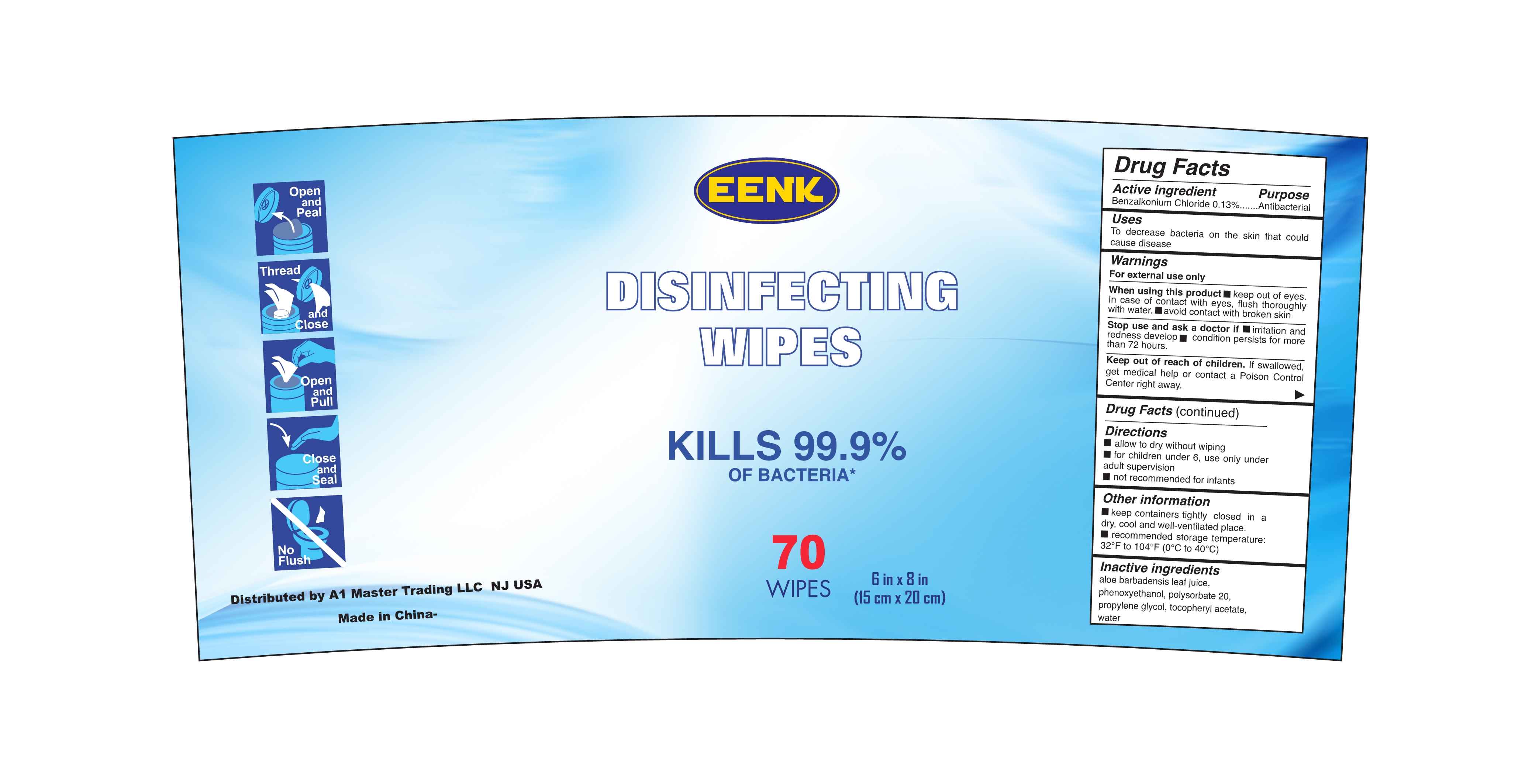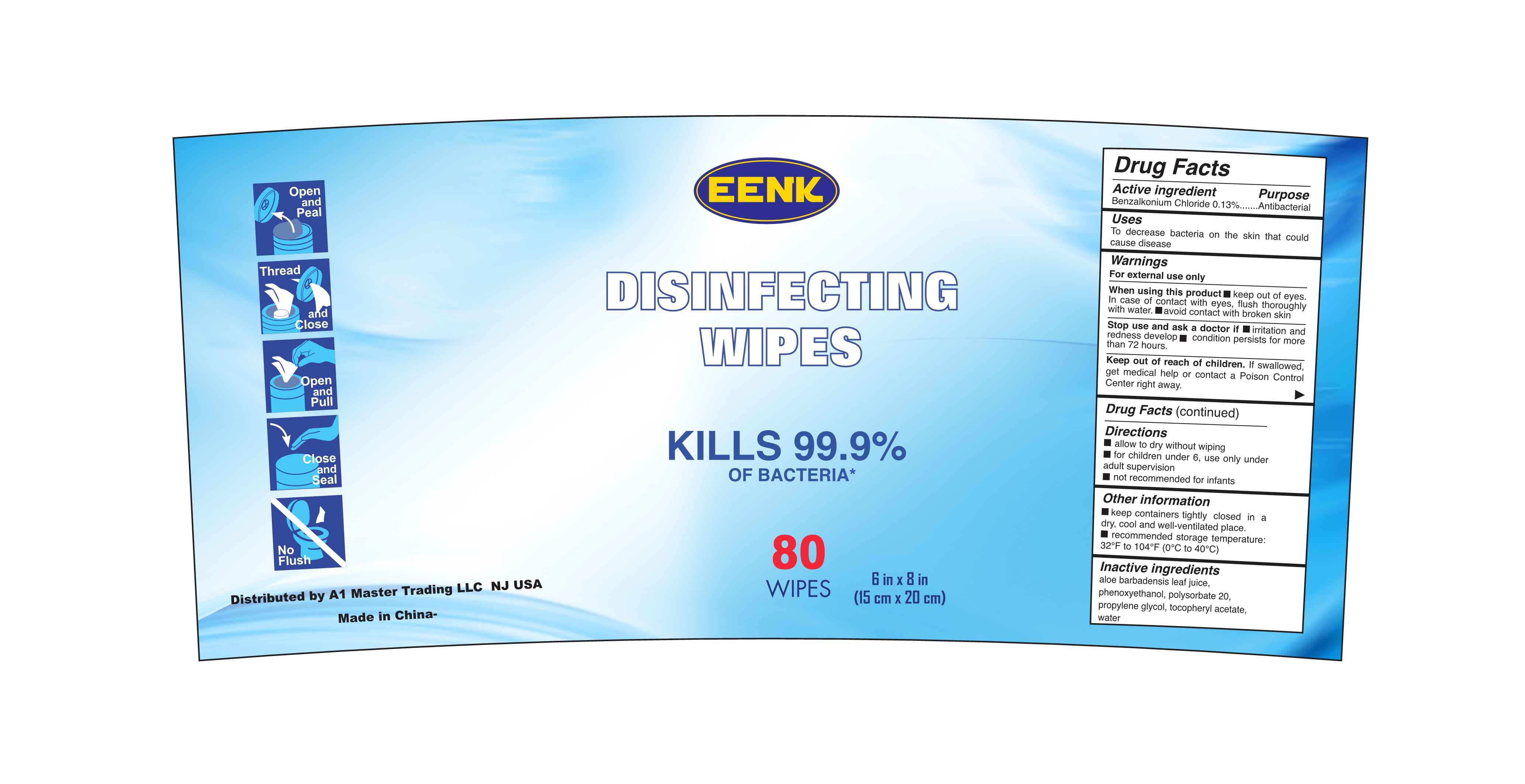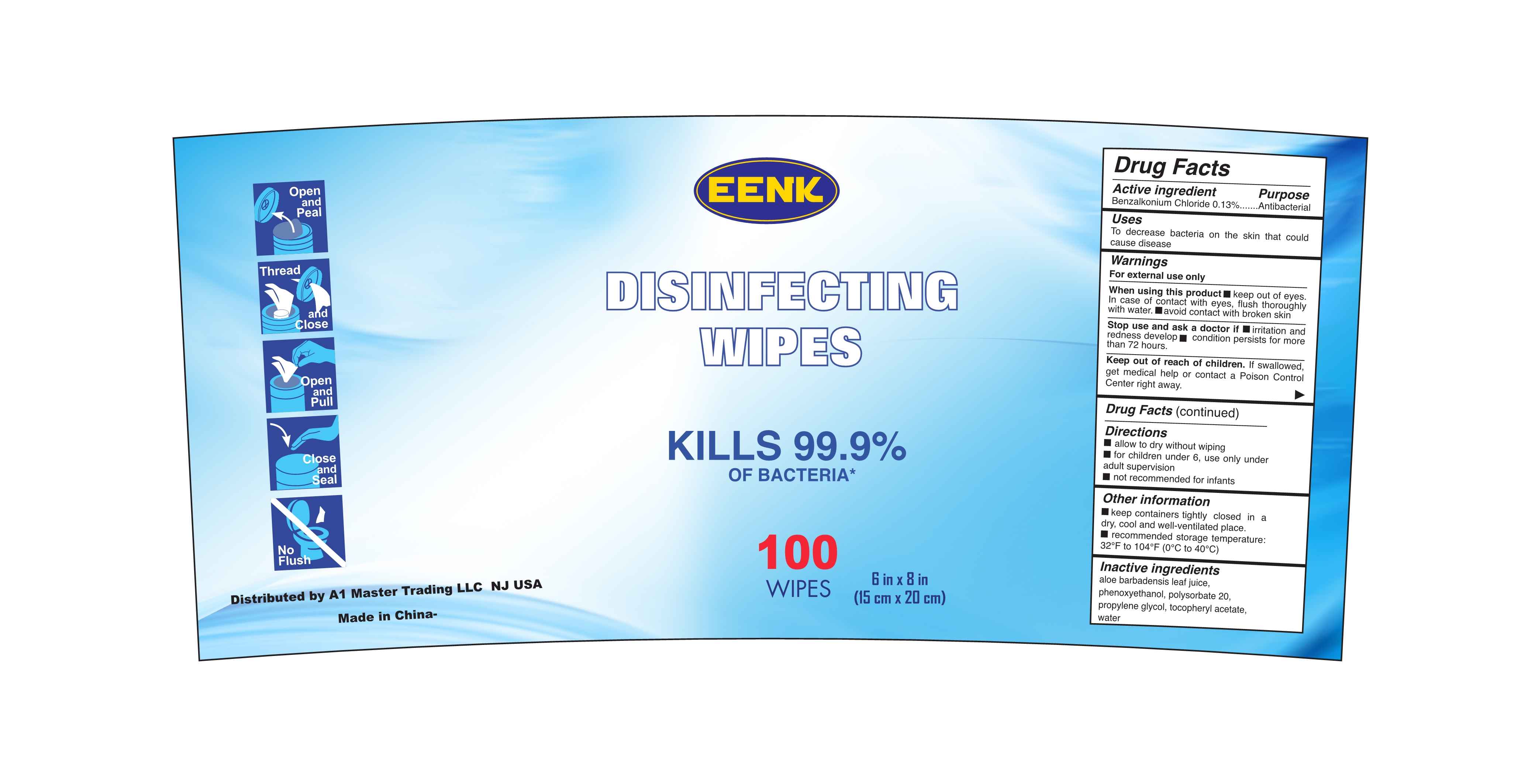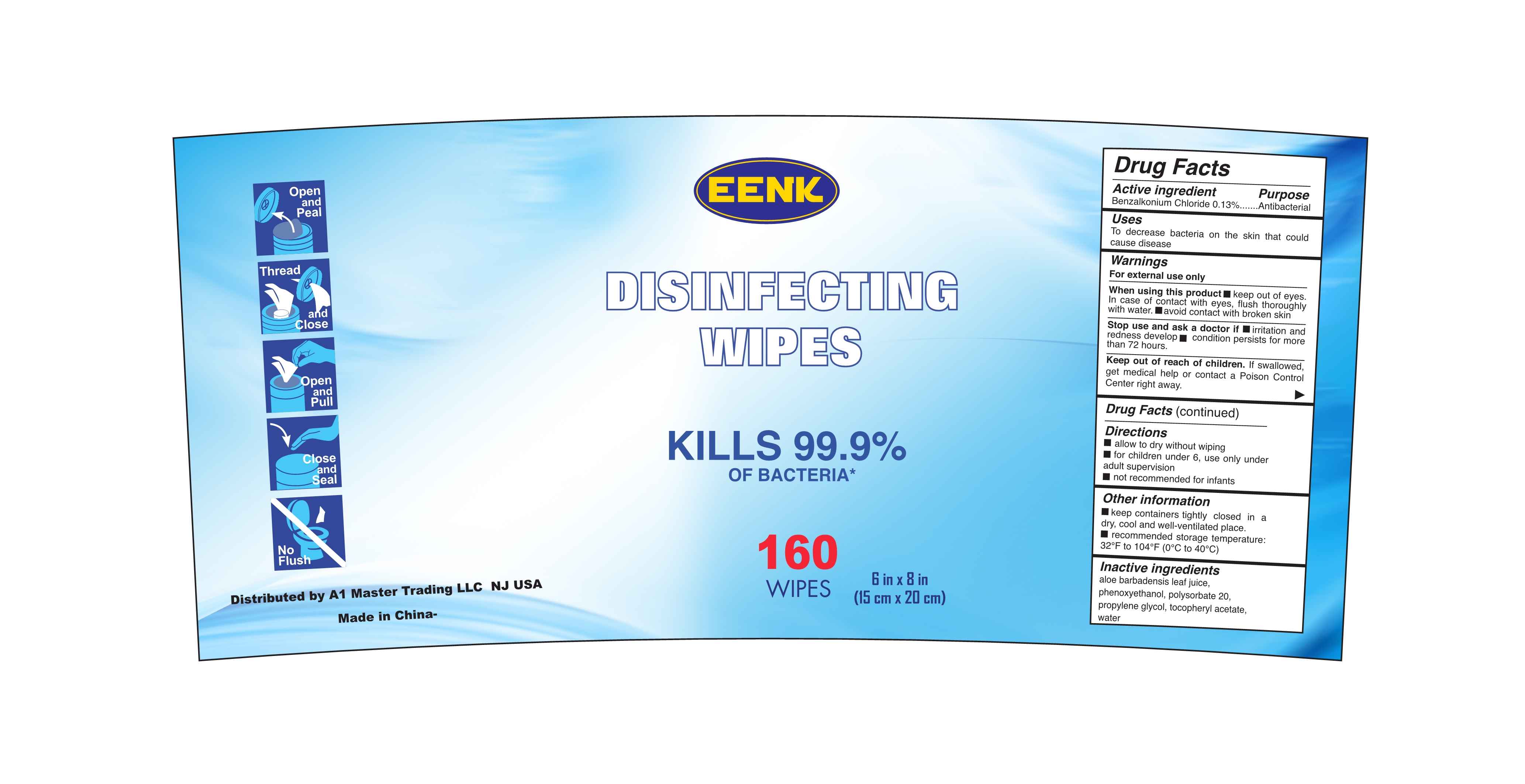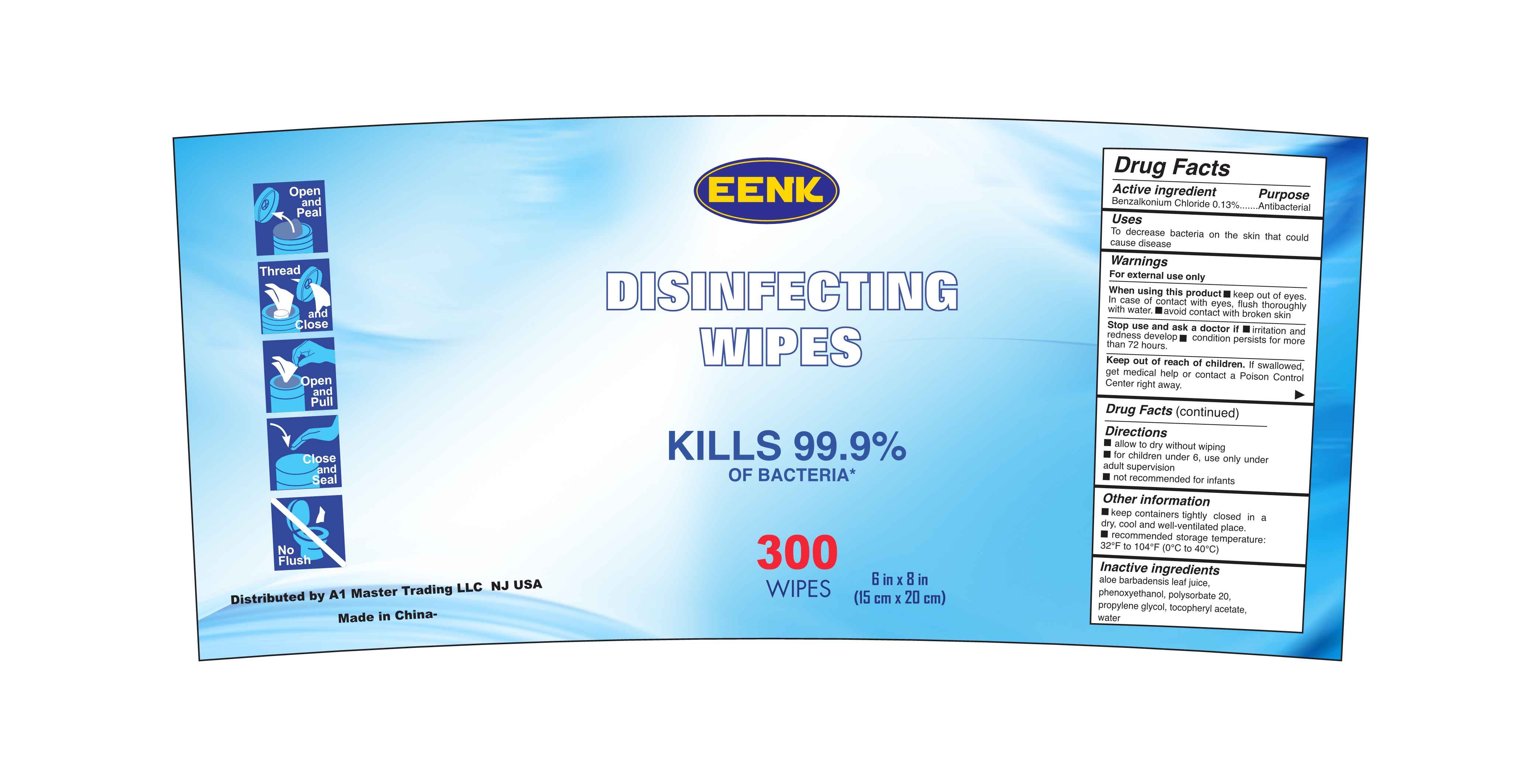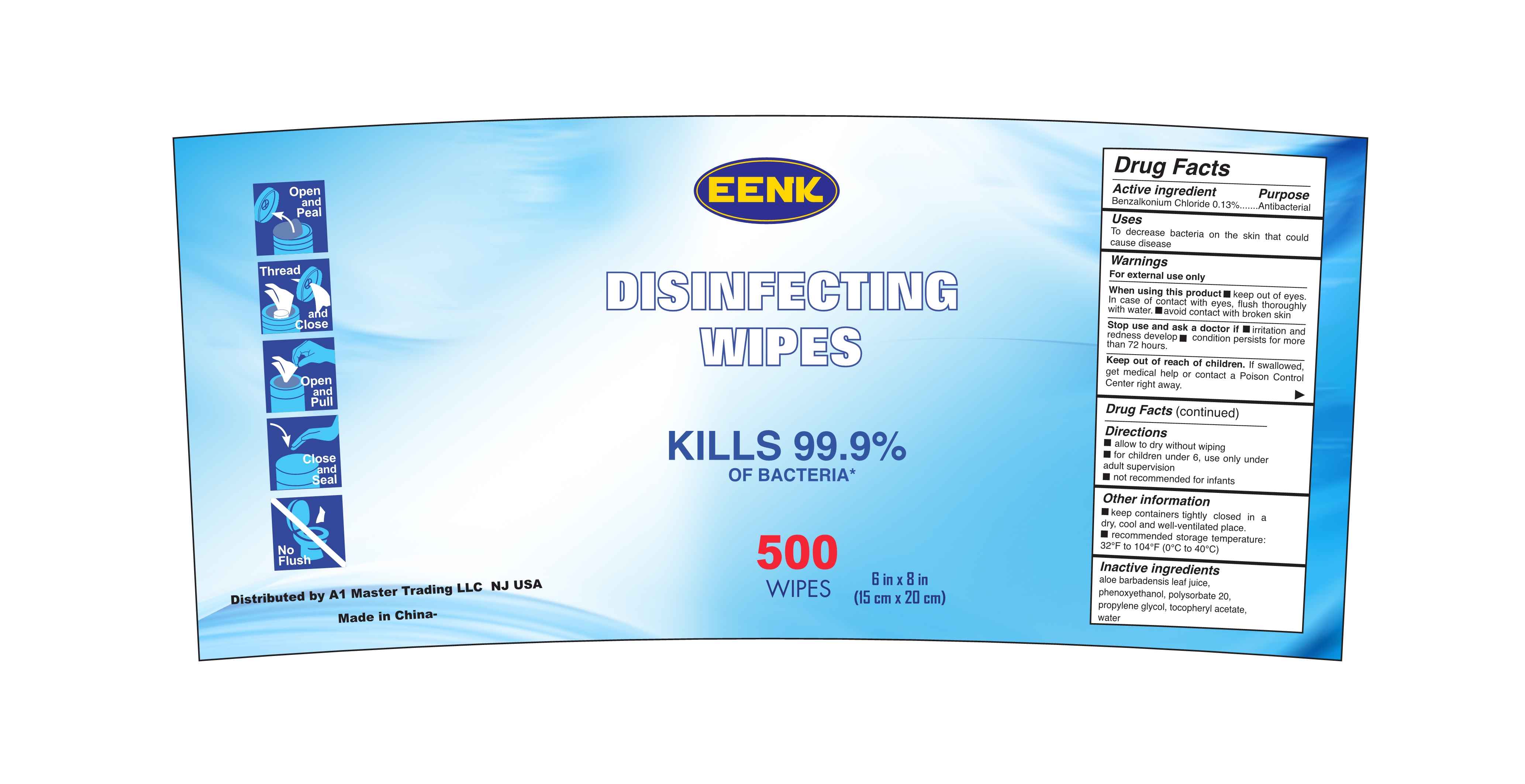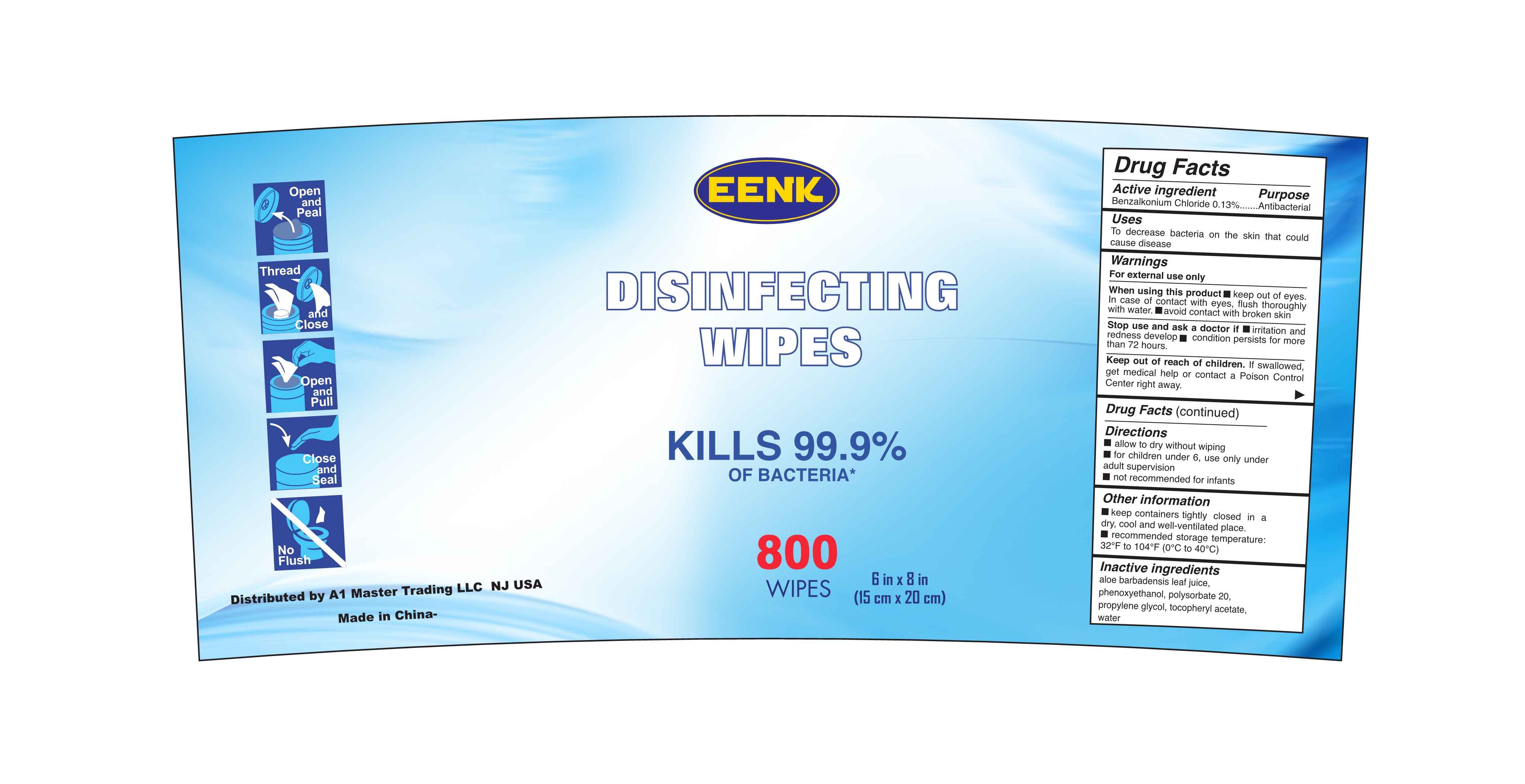 DRUG LABEL: ANTIBACTERIAL WIPES UNSCENTED
NDC: 80593-003 | Form: SOLUTION
Manufacturer: ZHANGZHOU WANSIKE ELECTRONICS CO., LTD
Category: otc | Type: HUMAN OTC DRUG LABEL
Date: 20201101

ACTIVE INGREDIENTS: BENZALKONIUM CHLORIDE 0.13 g/100 1
INACTIVE INGREDIENTS: .ALPHA.-TOCOPHEROL ACETATE; ALOE VERA LEAF; PHENOXYETHANOL; WATER; POLYSORBATE 20; PROPYLENE GLYCOL

80593-003
ANTIBACTERIAL WIPES UNSCENTED

Active Ingredient(s)

Benzalkonium Chloride 0.13%

Purpose

Antibacterial

Use

To decrease bacteria on the skin that could cause disease

Warnings

For external use only

When using this product
keep out of eyes.In case of contact with eyes, flush thoroughly with water.
avoid contact with broken skin

Stop use and ask a doctor if
irritation and redness develop
condition persists for more than 72 hours.

Keep out of reach of children. If swallowed, get medical help or contact a Poison

Control Center right away.

Do not use

/

WHEN USING

keep out of eyes.In case of contact with eyes, flush thoroughly with water.
avoid contact with broken skin

Stop use and ask a doctor if
irritation and redness develop
condition persists for more than 72 hours.

Keep out of reach of children. If swallowed, get medical help or contact a Poison

Control Center right away.

Stop use and ask a doctor if
irritation and redness develop
condition persists for more than 72 hours.

Keep out of reach of children. If swallowed, get medical help or contact a Poison

Control Center right away.

Directions

allow to dry without wiping
for children under 6, use only under adult supervision
not recommended for infants

Other information

keep containers tightly closed in a dry, cool and well-ventilated place.
recommended storage temperature: 32°F to 104°F (0°C to 40°C)

Inactive ingredients

aloe barbadensis leaf juice, phenoxyethanol, polysorbate 20, propylene glycol,

tocopheryl acetate, water